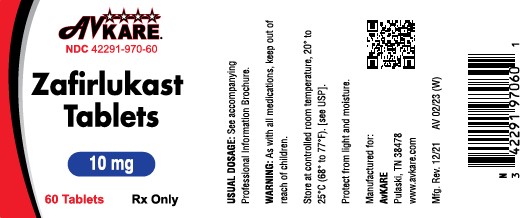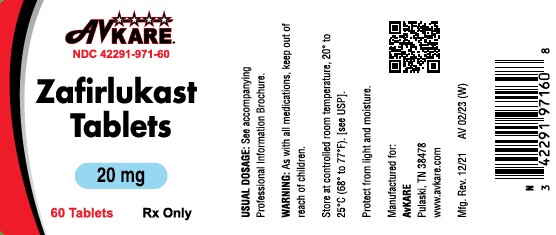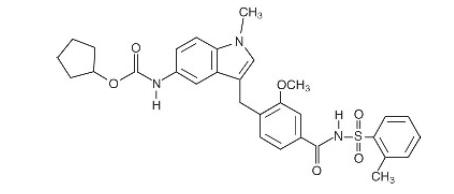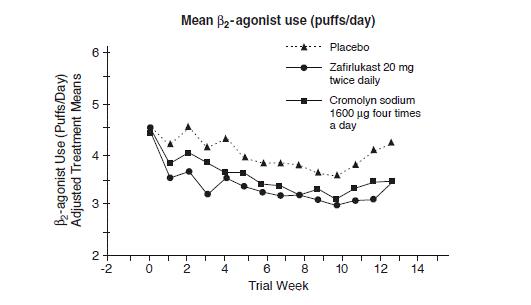 DRUG LABEL: Zafirlukast
NDC: 42291-970 | Form: TABLET, COATED
Manufacturer: AvKARE
Category: prescription | Type: HUMAN PRESCRIPTION DRUG LABEL
Date: 20250731

ACTIVE INGREDIENTS: ZAFIRLUKAST 10 mg/1 1
INACTIVE INGREDIENTS: CROSCARMELLOSE SODIUM; LACTOSE, UNSPECIFIED FORM; MAGNESIUM STEARATE; CELLULOSE, MICROCRYSTALLINE; POVIDONE; HYPROMELLOSES; TITANIUM DIOXIDE

Zafirlulkast Tablets
Rx Only

DESCRIPTION

Zafirlukast is a synthetic, selective peptide leukotriene receptor antagonist (LTRA), with the chemical name 4-(5-cyclopentyloxy-carbonylamino-1-methyl-indol-3-ylmethyl)-3-methoxy-N-o-tolylsulfonylbenzamide. The molecular weight of zafirlukast is 575.7 and the structural formula is:

The empirical formula is: C31H33N3O6S

Zafirlukast, a fine white to pale yellow amorphous powder, is practically insoluble in water. It is slightly soluble in methanol and freely soluble in tetrahydrofuran, dimethylsulfoxide, and acetone.

Zafirlukast is supplied as 10 and 20 mg tablets for oral administration.

Inactive Ingredients: Film-coated tablets containing croscarmellose sodium, lactose, magnesium stearate, microcrystalline cellulose, povidone, hypromellose, and titanium dioxide.

CLINICAL PHARMACOLOGY

Mechanism of Action:

Zafirlukast is a selective and competitive receptor antagonist of leukotriene D4 and E4 (LTD4 and LTE4), components of slow-reacting substance of anaphylaxis (SRSA). Cysteinyl leukotriene production and receptor occupation have been correlated with the pathophysiology of asthma, including airway edema, smooth muscle constriction, and altered cellular activity associated with the inflammatory process, which contribute to the signs and symptoms of asthma. Patients with asthma were found in one study to be 25 to 100 times more sensitive to the bronchoconstricting activity of inhaled LTD4 than nonasthmatic subjects.

In vitro studies demonstrated that zafirlukast antagonized the contractile activity of three leukotrienes (LTC4, LTD4 and LTE4) in conducting airway smooth muscle from laboratory animals and humans. Zafirlukast prevented intradermal LTD4-induced increases in cutaneous vascular permeability and inhibited inhaled LTD4-induced influx of eosinophils into animal lungs. Inhalational challenge studies in sensitized sheep showed that zafirlukast suppressed the airway responses to antigen; this included both the early- and late-phase response and the nonspecific hyperresponsiveness.

In humans, zafirlukast inhibited bronchoconstriction caused by several kinds of inhalational challenges. Pretreatment with single oral doses of zafirlukast inhibited the bronchoconstriction caused by sulfur dioxide and cold air in patients with asthma. Pretreatment with single doses of zafirlukast attenuated the early- and late-phase reaction caused by inhalation of various antigens such as grass, cat dander, ragweed, and mixed antigens in patients with asthma. Zafirlukast also attenuated the increase in bronchial hyperresponsiveness to inhaled histamine that followed inhaled allergen challenge.

Clinical Pharmacokinetics and Bioavailability:

Absorption

Zafirlukast is rapidly absorbed following oral administration. Peak plasma concentrations are generally achieved 3 hours after oral administration. The absolute bioavailability of zafirlukast is unknown. In two separate studies, one using a high fat and the other a high protein meal, administration of zafirlukast with food reduced the mean bioavailability by approximately 40%.

Distribution

Zafirlukast is more than 99% bound to plasma proteins, predominantly albumin. The degree of binding was independent of concentration in the clinically relevant range. The apparent steady-state volume of distribution (Vss/F) is approximately 70 L, suggesting moderate distribution into tissues. Studies in rats using radiolabeled zafirlukast indicate minimal distribution across the blood-brain barrier.

Metabolism

Zafirlukast is extensively metabolized. The most common metabolic products are hydroxylated metabolites which are excreted in the feces. The metabolites of zafirlukast identified in plasma are at least 90 times less potent as LTD4 receptor antagonists than zafirlukast in a standard in vitro test of activity. In vitro studies using human liver microsomes showed that the hydroxylated metabolites of zafirlukast excreted in the feces are formed through the cytochrome P450 2C9 (CYP2C9) pathway. Additional in vitro studies utilizing human liver microsomes show that zafirlukast inhibits the cytochrome P450 CYP3A4 and CYP2C9 isoenzymes at concentrations close to the clinically achieved total plasma concentrations (see Drug Interactions).

Excretion

The apparent oral clearance (CL/f) of zafirlukast is approximately 20 L/h. Studies in the rat and dog suggest that biliary excretion is the primary route of excretion. Following oral administration of radiolabeled zafirlukast to volunteers, urinary excretion accounts for approximately 10% of the dose and the remainder is excreted in feces. Zafirlukast is not detected in urine.

In the pivotal bioequivalence study, the mean terminal half-life of zafirlukast is approximately 10 hours in both normal adult subjects and patients with asthma. In other studies, the mean plasma half-life of zafirlukast ranged from approximately 8 to 16 hours in both normal subjects and patients with asthma. The pharmacokinetics of zafirlukast are approximately linear over the range from 5 mg to 80 mg. Steady-state plasma concentrations of zafirlukast are proportional to the dose and predictable from single-dose pharmacokinetic data. Accumulation of zafirlukast in the plasma following twice-daily dosing is approximately 45%.

The pharmacokinetic parameters of zafirlukast 20 mg administered as a single dose to 36 male volunteers are shown with the table below.

Mean (% Coefficient of Variation) pharmacokinetic parameters of zafirlukast following single 20 mg oral dose administration to male volunteers (n=36)
Cmax ng/ml |  | tmax^1 h | AUC ng•h/mL | t1/2 h | CL/f L/h
326 (31.0) |  | 2 (0.5 - 5.0) | 1137 (34) | 13.3 (75.6) | 19.4 (32)

1.Median and range

Special Populations

Gender: The pharmacokinetics of zafirlukast are similar in males and females. Weight-adjusted apparent oral clearance does not differ due to gender.

Race: No differences in the pharmacokinetics of zafirlukast due to race have been observed.

Elderly: The apparent oral clearance of zafirlukast decreases with age. In patients above 65 years of age, there is an approximately 2 to 3 fold greater Cmax and AUC compared to young adult patients.

Children: Following administration of a single 20 mg dose of zafirlukast to 20 boys and girls between 7 and 11 years of age, and in a second study, to 29 boys and girls between 5 and 6 years of age, the following pharmacokinetic parameters were obtained:

Parameter | Children age 5 to 6 years Mean (% Coefficient of Variation) | Children age 7 to 11 years Mean (% Coefficient of Variation)
Cmax (ng/mL) | 756 (39%) | 601 (45%)
AUC (ng•h/mL) | 2458 (34%) | 2027 (38%)
tmax (h) | 2.1 (61%) | 2.5 (55%)
CL/f (L/h) | 9.2 (37%) | 11.4 (42%)

Weight unadjusted apparent clearance was 11.4 L/h (42%) in the 7 to 11 year old children and 9.2 L/h (37%) in the 5 to 6 year old children, which resulted in greater systemic drug exposures than that obtained in adults for an identical dose. To maintain similar exposure levels in children compared to adults, a dose of 10 mg twice daily is recommended in children 5 to 11 years of age (see DOSAGE AND ADMINISTRATION).

Zafirlukast disposition was unchanged after multiple dosing (20 mg twice daily) in children and the degree of accumulation in plasma was similar to that observed in adults.

Hepatic Insufficiency: In a study of patients with hepatic impairment (biopsy-proven cirrhosis), there was a reduced clearance of zafirlukast resulting in a 50 to 60% greater Cmax and AUC compared to normal subjects.

Renal Insufficiency: Based on a cross-study comparison, there are no apparent differences in the pharmacokinetics of zafirlukast between renally-impaired patients and normal subjects.

Drug-Drug Interactions: The following drug interaction studies have been conducted with zafirlukast (see PRECAUTIONS, Drug Interactions).

- Coadministration of multiple doses of zafirlukast (160 mg/day) to steady-state with a single 25 mg dose of warfarin (a substrate of CYP2C9) resulted in a significant increase in the mean AUC (+63%) and half-life (+36%) of S-warfarin. The mean prothrombin time increased by approximately 35%. The pharmacokinetics of zafirlukast were unaffected by coadministration with warfarin.
- Coadministration of zafirlukast (80 mg/day) at steady-state with a single dose of a liquid theophylline preparation (6 mg/kg) in 13 asthmatic patients, 18 to 44 years of age, resulted in decreased mean plasma concentrations of zafirlukast by approximately 30%, but no effect on plasma theophylline concentrations was observed.
- Coadministration of zafirlukast (20 mg/day) or placebo at steady-state with a single dose of sustained release theophylline preparation (16 mg/kg) in 16 healthy boys and girls (6 through 11 years of age) resulted in no significant differences in the pharmacokinetic parameters of theophylline.
- Coadministration of zafirlukast dosed at 40 mg twice daily in a single-blind, parallel-group, 3-week study in 39 healthy female subjects taking oral contraceptives, resulted in no significant effect on ethinyl estradiol plasma concentrations or contraceptive efficacy.
- Coadministration of zafirlukast (40 mg/day) with aspirin (650 mg four times daily) resulted in mean increased plasma concentrations of zafirlukast by approximately 45%.
- Coadministration of a single dose of zafirlukast (40 mg) with erythromycin (500 mg three times daily for 5 days) to steady-state in 11 asthmatic patients resulted in decreased mean plasma concentrations of zafirlukast by approximately 40% due to a decrease in zafirlukast bioavailability.
- Coadministration of zafirlukast with fluconazole, a moderate CYP2C9 inhibitor, resulted in increased plasma levels of zafirlukast, by approximately 58% (90% CI:28, 95). The clinical significance of this interaction is unknown. Zafirlukast exposure is likely to be increased by other moderate and strong CYP2C9 inhibitors. Coadministration of zafirlukast with itraconazole, a strong CYP3A4 inhibitor, caused no change in plasma levels of zafirlukast.

Clinical Studies:

Three U.S. double-blind, randomized, placebo-controlled, 13-week clinical trials in 1380 adults and children 12 years of age and older with mild-to-moderate asthma demonstrated that zafirlukast improved daytime asthma symptoms, nighttime awakenings, mornings with asthma symptoms, rescue beta2-agonist use, FEV1, and morning peak expiratory flow rate. In these studies, the patients had a mean baseline FEV1 of approximately 75% of predicted normal and a mean baseline beta2-agonist requirement of approximately 4 to 5 puffs of albuterol per day. The results of the largest of the trials are shown in the table below.

Mean Change from Baseline at Study End Point
 | Zafirlukast 20 mg twice daily N=514 | Placebo N=248
Daytime Asthma symptom score (0-3 scale) | -0.44^1 | -0.25
Nighttime Awakenings (number per week) | -1.27^1 | -0.43
Mornings with Asthma Symptoms (days per week) | -1.32^1 | -0.75
Rescue β2-agonist use (puffs per day) | -1.15^1 | -0.24
FEV1 (L) | +0.15^1 | +0.05
Morning PEFR (L/min) | +22.06^1 | +7.63
Evening PEFR (L/min) | +13.12 | +10.14

1. p<0.05, compared to placebo

In a second and smaller study, the effect of zafirlukast on most efficacy parameters was comparable to the active control (inhaled cromolyn sodium 1600 mcg four times per day) and superior to placebo at end point for decreasing rescue beta2-agonist use (figure below).

In these trials, improvement in asthma symptoms occurred within one week of initiating treatment with zafirlukast. The role of zafirlukast in the management of patients with more severe asthma, patients receiving antiasthma therapy other than as-needed, inhaled beta2-agonists, or as an oral or inhaled corticosteroid-sparing agent remains to be fully characterized.

INDICATIONS AND USAGE

Zafirlukast is indicated for the prophylaxis and chronic treatment of asthma in adults and children 5 years of age and older.

CONTRAINDICATIONS

Zafirlukast is contraindicated in patients who are hypersensitive to zafirlukast or any of its inactive ingredients.

Zafirlukast is contraindicated in patients with hepatic impairment including hepatic cirrhosis.

WARNINGS

Hepatotoxicity:

Cases of life-threatening hepatic failure have been reported in patients treated with zafirlukast. Cases of liver injury without other attributable cause have been reported from post-marketing adverse event surveillance of patients who have received the recommended dose of zafirlukast (40 mg/day). In most, but not all post-marketing reports, the patient's symptoms abated and the liver enzymes returned to normal or near normal after stopping zafirlukast. In rare cases, patients have either presented with fulminant hepatitis or progressed to hepatic failure, liver transplantation and death. In extremely rare post-marketing cases, no clinical symptoms or signs suggestive of liver dysfunction were reported to precede the latter observations.

Physicians may consider the value of liver function testing. Periodic serum transaminase testing has not proven to prevent serious injury but it is generally believed that early detection of drug-induced hepatic injury along with immediate withdrawal of the suspect drug enhances the likelihood for recovery.

Patients should be advised to be alert for signs and symptoms of liver dysfunction (e.g., right upper quadrant abdominal pain, nausea, fatigue, lethargy, pruritus, jaundice, flu-like symptoms, and anorexia) and to contact their physician immediately if they occur. Ongoing clinical assessment of patients should govern physician interventions, including diagnostic evaluations and treatment.

If liver dysfunction is suspected based upon clinical signs or symptoms (e.g., right upper quadrant abdominal pain, nausea, fatigue, lethargy, pruritus, jaundice, flu-like symptoms, anorexia, and enlarged liver), zafirlukast should be discontinued.

Liver function tests, in particular serum ALT, should be measured immediately and the patient managed accordingly. If liver function tests are consistent with hepatic dysfunction, zafirlukast therapy should not be resumed. Patients in whom zafirlukast was withdrawn because of hepatic dysfunction where no other attributable cause is identified should not be re-exposed to zafirlukast (see PRECAUTIONS, Information for Patients and ADVERSE REACTIONS).

Bronchospasm:

Zafirlukast is not indicated for use in the reversal of bronchospasm in acute asthma attacks, including status asthmaticus. Therapy with zafirlukast can be continued during acute exacerbations of asthma.

Concomitant Warfarin Administration:

Coadministration of zafirlukast with warfarin results in a clinically significant increase in prothrombin time (PT). Patients on oral warfarin anticoagulant therapy and zafirlukast should have their prothrombin times monitored closely and anticoagulant dose adjusted accordingly (see PRECAUTIONS, Drug Interactions).

PRECAUTIONS

Information for Patients:

Patients should be told that a rare side effect of zafirlukast is hepatic dysfunction, and to contact their physician immediately if they experience symptoms of hepatic dysfunction (e.g., right upper quadrant abdominal pain, nausea, fatigue, lethargy, pruritus, jaundice, flu-like symptoms, and anorexia). Liver failure resulting in liver transplantation and death has occurred in patients taking zafirlukast (see WARNINGS, Hepatotoxicity and ADVERSE REACTIONS).

Zafirlukast is indicated for the chronic treatment of asthma and should be taken regularly as prescribed, even during symptom-free periods. Zafirlukast is not a bronchodilator and should not be used to treat acute episodes of asthma. Patients receiving zafirlukast should be instructed not to decrease the dose or stop taking any other antiasthma medications unless instructed by a physician. Patients should be instructed to notify their physician if neuropsychiatric events occur while using zafirlukast (see PRECAUTIONS, Neuropsychiatric Events). Women who are breast-feeding should be instructed not to take zafirlukast (see PRECAUTIONS, Nursing Mothers). Alternative antiasthma medication should be considered in such patients.

The bioavailability of zafirlukast may be decreased when taken with food. Patients should be instructed to take zafirlukast at least 1 hour before or 2 hours after meals.

Eosinophilic Conditions:

In rare cases, patients with asthma on zafirlukast may present with systemic eosinophilia, eosinophilic pneumonia, or clinical features of vasculitis consistent with Churg-Strauss syndrome, a condition which is often treated with systemic steroid therapy. Physicians should be alert to eosinophilia, vasculitic rash, worsening pulmonary symptoms, cardiac complications, and/or neuropathy presenting in their patients. These events have usually, but not always, been associated with reductions and/or withdrawal of steroid therapy. The possibility that zafirlukast may be associated with emergence of Churg-Strauss syndrome can neither be excluded nor established (see ADVERSE REACTIONS).

Neuropsychiatric Events:

Neuropsychiatric events have been reported in adult, adolescent and pediatric patients taking zafirlukast. Post-marketing reports with zafirlukast include insomnia and depression. The clinical details of some post-marketing reports involving zafirlukast appear consistent with a drug-induced effect. Patients and prescribers should be alert for neuropsychiatric events. Patients should be instructed to notify their prescriber if these changes occur. Prescribers should carefully evaluate the risks and benefits of continuing treatment with zafirlukast if such events occur (see ADVERSE REACTIONS).

Drug Interactions:

In a drug interaction study in 16 healthy male volunteers, coadministration of multiple doses of zafirlukast (160 mg/day) to steady-state with a single 25 mg dose of warfarin resulted in a significant increase in the mean AUC (+ 63%) and half-life (+36%) of S-warfarin. The mean prothrombin time (PT) increased by approximately 35%. This interaction is probably due to an inhibition by zafirlukast of the cytochrome P450 2C9 isoenzyme system. Patients on oral warfarin anticoagulant therapy and zafirlukast should have their prothrombin times monitored closely and anticoagulant dose adjusted accordingly (see WARNINGS, Concomitant Warfarin Administration). No formal drug-drug interaction studies with zafirlukast and other drugs known to be metabolized by the cytochrome P450 2C9 isoenzyme (e.g., tolbutamide, phenytoin, carbamazepine) have been conducted; however, care should be exercised when zafirlukast is coadministered with these drugs .

In a drug interaction study in 11 asthmatic patients, coadministration of a single dose of zafirlukast (40 mg) with erythromycin (500 mg three times daily for 5 days) to steady-state resulted in decreased mean plasma levels of zafirlukast by approximately 40% due to a decrease in zafirlukast bioavailability.

Coadministration of zafirlukast (20 mg/day) or placebo at steady-state with a single dose of sustained release theophylline preparation (16 mg/kg) in 16 healthy boys and girls (6 through 11 years of age) resulted in no significant differences in the pharmacokinetic parameters of theophylline.

Coadministration of zafirlukast (80 mg/day) at steady-state with a single dose of a liquid theophylline preparation (6 mg/kg) in 13 asthmatic patients, 18 to 44 years of age, resulted in decreased mean plasma levels of zafirlukast by approximately 30%, but no effect on plasma theophylline levels was observed.

Rare cases of patients experiencing increased theophylline levels with or without clinical signs or symptoms of theophylline toxicity after the addition of zafirlukast to an existing theophylline regimen have been reported. The mechanism of the interaction between zafirlukast and theophylline in these patients is unknown (see ADVERSE REACTIONS).

Coadministration of zafirlukast (40 mg/day) with aspirin (650 mg four times daily) resulted in mean increased plasma levels of zafirlukast by approximately 45%.

In a single-blind, parallel-group, 3-week study in 39 healthy female subjects taking oral contraceptives, 40 mg twice daily of zafirlukast had no significant effect on ethinyl estradiol plasma concentrations or contraceptive efficacy.

Coadministration of zafirlukast with fluconazole, a moderate CYP2C9 inhibitor, resulted in increased plasma levels of zafirlukast, by approximately 58% (90% CI:28, 95). The clinical significance of this interaction is unknown. Zafirlukast exposure is likely to be increased by other moderate and strong CYP2C9 inhibitors. Coadministration of zafirlukast with itraconazole, a strong CYP3A4 inhibitor, caused no change in plasma levels of zafirlukast.

No other formal drug-drug interaction studies between zafirlukast and marketed drugs known to be metabolized by the P450 3A4 (CYP3A4) isoenzyme (e.g., dihydropyridine calcium-channel blockers, cyclosporin, cisapride) have been conducted. As zafirlukast is known to be an inhibitor of CYP3A4 in vitro, it is reasonable to employ appropriate clinical monitoring when these drugs are coadministered with zafirlukast.

Carcinogenesis, Mutagenesis, Impairment of Fertility:

In two-year carcinogenicity studies, zafirlukast was administered at dietary doses of 10, 100, and 300 mg/kg to mice and 40, 400, and 2000 mg/kg to rats. Male mice at an oral dose of 300 mg/kg/day (approximately 30 times the maximum recommended daily oral dose in adults and in children on a mg/m^2 basis) showed an increased incidence of hepatocellular adenomas; female mice at this dose showed a greater incidence of whole body histocytic sarcomas. Male and female rats at an oral dose of 2000 mg/kg/day (resulting in approximately 160 times the exposure to drug plus metabolites from the maximum recommended daily oral dose in adults and in children based on a comparison of the plasma area-under the curve [AUC] values) of zafirlukast showed an increased incidence of urinary bladder transitional cell papillomas. Zafirlukast was not tumorigenic at oral doses up to 100 mg/kg (approximately 10 times the maximum recommended daily oral dose in adults and in children on a mg/m^2 basis) in mice and at oral doses up to 400 mg/kg (resulting in approximately 140 times the exposure to drug plus metabolites from the maximum recommended daily oral dose in adults and in children based on a comparison of the plasma AUC values) in rats. The clinical significance of these findings for the long-term use of zafirlukast is unknown.

Zafirlukast showed no evidence of mutagenic potential in the reverse microbial assay, in 2 forward point mutation (CHO-HGPRT and mouse lymphoma) assays or in two assays for chromosomal aberrations (the in vitro human peripheral blood lymphocyte clastogenic assay and the in vivo rat bone marrow micronucleus assay).

No evidence of impairment of fertility and reproduction was seen in male and female rats treated with zafirlukast at oral doses up to 2000 mg/kg (approximately 410 times the maximum recommended daily oral dose in adults on a mg/m^2 basis).

Pregnancy Category B:

No teratogenicity was observed at oral doses up to 1600 mg/kg/day in mice (approximately 160 times the maximum recommended daily oral dose in adults on a mg/m^2 basis), up to 2000 mg/kg/day in rats (approximately 410 times the maximum recommended daily oral dose in adults on a mg/m^2 basis) and up to 2000 mg/kg/day in cynomolgus monkeys (which resulted in approximately 20 times the exposure to drug plus metabolites compared to that from the maximum recommended daily oral dose in adults based on comparison of the AUC values). At an oral dose of 2000 mg/kg/day in rats, maternal toxicity and deaths were seen with increased incidence of early fetal resorption. Spontaneous abortions occurred in cynomolgus monkeys at the maternally toxic oral dose of 2000 mg/kg/day. There are no adequate and well-controlled trials in pregnant women. Because animal reproductive studies are not always predictive of human response, zafirlukast should be used during pregnancy only if clearly needed.

Nursing Mothers:

Zafirlukast is excreted in breast milk. Following repeated 40 mg twice-a-day dosing in healthy women, average steady-state concentrations of zafirlukast in breast milk were 50 ng/mL compared to 255 ng/mL in plasma. Because of the potential for tumorigenicity shown for zafirlukast in mouse and rat studies and the enhanced sensitivity of neonatal rats and dogs to the adverse effects of zafirlukast, zafirlukast should not be administered to mothers who are breast-feeding.

Pediatric Use:

The safety of zafirlukast at doses of 10 mg twice daily has been demonstrated in 205 pediatric patients 5 through 11 years of age in placebo-controlled trials lasting up to six weeks and with 179 patients in this age range participating in 52 weeks of treatment in an open label extension.

The effectiveness of zafirlukast for the prophylaxis and chronic treatment of asthma in pediatric patients 5 through 11 years of age is based on an extrapolation of the demonstrated efficacy of zafirlukast in adults with asthma and the likelihood that the disease course, and pathophysiology and the drug's effect are substantially similar between the two populations. The recommended dose for the patients 5 through 11 years of age is based upon a cross-study comparison of the pharmacokinetics of zafirlukast in adults and pediatric subjects, and on the safety profile of zafirlukast in both adult and pediatric patients at doses equal to or higher than the recommended dose.

The safety and effectiveness of zafirlukast for pediatric patients less than 5 years of age has not been established. The effect of zafirlukast on growth in children has not been determined.

Geriatric Use:

Based on cross-study comparison, the clearance of zafirlukast is reduced in patients 65 years of age and older such that Cmax and AUC are approximately 2- to 3-fold greater than those of younger patients (see DOSAGE AND ADMINISTRATION and CLINICAL PHARMACOLOGY).

A total of 8094 patients were exposed to zafirlukast in North American and European short-term placebo-controlled clinical trials. Of these, 243 patients were elderly (age 65 years and older). No overall difference in adverse events was seen in the elderly patients, except for an increase in the frequency of infections among zafirlukast-treated elderly patients compared to placebo-treated elderly patients (7.0% vs. 2.9%). The infections were not severe, occurred mostly in the lower respiratory tract, and did not necessitate withdrawal of therapy.

An open-label, uncontrolled, 4-week trial of 3759 asthma patients compared the safety and efficacy of zafirlukast 20 mg given twice daily in three patient age groups, adolescents (12 to 17 years), adults (18 to 65 years), and elderly (greater than 65 years). A higher percentage of elderly patients (n=384) reported adverse events when compared to adults and adolescents. These elderly patients showed less improvement in efficacy measures. In the elderly patients, adverse events occurring in greater than 1% of the population included headache (4.7%), diarrhea and nausea (1.8%), and pharyngitis (1.3%). The elderly reported the lowest percentage of infections of all three age groups in this study.

ADVERSE REACTIONS

Adults and Children 12 years of age and older

The safety database for zafirlukast consists of more than 4000 healthy volunteers and patients who received zafirlukast, of which 1723 were asthmatics enrolled in trials of 13 weeks duration or longer. A total of 671 patients received zafirlukast for 1 year or longer. The majority of the patients were 18 years of age or older; however, 222 patients between the age of 12 and 18 years received zafirlukast.

A comparison of adverse events reported by ≥1% of zafirlukast-treated patients, and at rates numerically greater than in placebo-treated patients, is shown for all trials in the table below.

Adverse Event | Zafirlukast N=4058 | Placebo N=2032
Headache | 12.9% | 11.7%
Infection | 3.5% | 3.4%
Nausea | 3.1% | 2.0%
Diarrhea | 2.8% | 2.1%
Pain (generalized) | 1.9% | 1.7%
Asthenia | 1.8% | 1.6%
Abdominal Pain | 1.8% | 1.1%
Accidental Injury | 1.6% | 1.5%
Dizziness | 1.6% | 1.5%
Myalgia | 1.6% | 1.5%
Fever | 1.6% | 1.1%
Back Pain | 1.5% | 1.2%
Vomiting | 1.5% | 1.1%
SGPT Elevation | 1.5% | 1.1%
Dyspepsia | 1.3% | 1.2%

The frequency of less common adverse events was comparable between zafirlukast and placebo.

Rarely, elevations of one or more liver enzymes have occurred in patients receiving zafirlukast in controlled clinical trials. In clinical trials, most of these have been observed at doses four times higher than the recommended dose. The following hepatic events (which have occurred predominantly in females) have been reported from postmarketing adverse event surveillance of patients who have received the recommended dose of zafirlukast (40 mg/day): cases of symptomatic hepatitis (with or without hyperbilirubinemia) without other attributable cause; and rarely, hyperbilirubinemia without other elevated liver function tests. In most, but not all postmarketing reports, the patient's symptoms abated and the liver enzymes returned to normal or near normal after stopping zafirlukast. In rare cases, patients have presented with fulminant hepatitis or progressed to hepatic failure, liver transplantation and death (see WARNINGS, Hepatotoxicity and PRECAUTIONS, Information for Patients)

In clinical trials, an increased proportion of zafirlukast patients over the age of 55 years reported infections as compared to placebo-treated patients. A similar finding was not observed in other age groups studied. These infections were mostly mild or moderate in intensity and predominantly affected the respiratory tract. Infections occurred equally in both sexes, were dose-proportional to total milligrams of zafirlukast exposure, and were associated with coadministration of inhaled corticosteroids. The clinical significance of this finding is unknown.

In rare cases, patients with asthma on zafirlukast may present with systemic eosinophilia, eosinophilic pneumonia, or clinical features of vasculitis consistent with Churg-Strauss syndrome, a condition which is often treated with systemic steroid therapy. Physicians should be alert to eosinophilia, vasculitic rash, worsening pulmonary symptoms, cardiac complications, and/or neuropathy presenting in their patients. These events have usually, but not always, been associated with reductions and/or withdrawal of steroid therapy. The possibility that zafirlukast may be associated with emergence of Churg-Strauss syndrome can neither be excluded nor established (see PRECAUTIONS, Eosinophilic Conditions).

Neuropsychiatric adverse events, including insomnia and depression, have been reported in association with zafirlukast therapy (see PRECAUTIONS, Neuropsychiatric Events). Hypersensitivity reactions, including urticaria, angioedema and rashes, with or without blistering, have also been reported in association with zafirlukast therapy. Additionally, there have been reports of patients experiencing agranulocytosis, bleeding, bruising, or edema, arthralgia, myalgia, malaise, and pruritus in association with zafirlukast therapy.

Rare cases of patients experiencing increased theophylline levels with or without clinical signs or symptoms of theophylline toxicity after the addition of zafirlukast to an existing theophylline regimen have been reported. The mechanism of the interaction between zafirlukast and theophylline in these patients is unknown and not predicted by available in vitro metabolism data and the results of two clinical drug interaction studies (see CLINICAL PHARMACOLOGY and PRECAUTIONS, Drug Interactions).

Pediatric Patients 5 through 11 years of age

Zafirlukast has been evaluated for safety in 788 pediatric patients 5 through 11 years of age. Cumulatively, 313 pediatric patients were treated with zafirlukast 10 mg twice daily or higher for at least 6 months, and 113 of them were treated for one year or longer in clinical trials. The safety profile of zafirlukast 10 mg twice daily-versus placebo in the 4- and 6-week double-blind trials was generally similar to that observed in the adult clinical trials with zafirlukast 20 mg twice daily.

In pediatric patients receiving zafirlukast in multi-dose clinical trials, the following events occurred with a frequency of ≥2% and more frequently than in pediatric patients who received placebo, regardless of causality assessment: headache (4.5 vs. 4.2%) and abdominal pain (2.8 vs. 2.3%).

The post-marketing experience in this age group is similar to that seen in adults, including hepatic dysfunction, which may lead to liver failure.

To report SUSPECTED ADVERSE REACTIONS, contact AvKARE at 1-855-361-3993 or FDA at 1-800-FDA-1088 or www.fda.gov/ medwatch.

OVERDOSAGE

No deaths occurred at oral zafirlukast doses of 2000 mg/kg in mice (approximately 210 times the maximum recommended daily oral dose in adults and children on a mg/m^2 basis), 2000 mg/kg in rats (approximately 420 times the maximum recommended daily oral dose in adults and children on a mg/m^2 basis), and 500 mg/kg in dogs (approximately 350 times the maximum recommended daily oral dose in adults and children on a mg/m^2 basis).

Overdosage with zafirlukast has been reported in four patients surviving reported doses as high as 200 mg. The predominant symptoms reported following zafirlukast overdose were rash and upset stomach. There were no acute toxic effects in humans that could be consistently ascribed to the administration of zafirlukast. It is reasonable to employ the usual supportive measures in the event of an overdose; e.g., remove unabsorbed material from the gastrointestinal tract, employ clinical monitoring, and institute supportive therapy, if required.

DOSAGE AND ADMINISTRATION

Because food can reduce the bioavailability of zafirlukast, zafirlukast should be taken at least 1 hour before or 2 hours after meals.

Adults and Children 12 years of age and older

The recommended dose of zafirlukast in adults and children 12 years and older is 20 mg twice daily.

Pediatric Patients 5 through 11 years of age

The recommended dose of zafirlukast in children 5 through 11 years of age is 10 mg twice daily.

Elderly Patients

Based on cross-study comparisons, the clearance of zafirlukast is reduced in elderly patients (65 years of age and older), such that Cmax and AUC are approximately twice those of younger adults. In clinical trials, a dose of 20 mg twice daily was not associated with an increase in the overall incidence of adverse events or withdrawals because of adverse events in elderly patients.

Patients with Hepatic Impairment

Zafirlukast is contraindicated in patients with hepatic impairment including hepatic cirrhosis (see CONTRAINDICATIONS). The clearance of zafirlukast is reduced in patients with stable alcoholic cirrhosis such that the Cmax and AUC are approximately 50 to 60% greater than those of normal adults. Zafirlukast has not been evaluated in patients with hepatitis or in long-term studies of patients with cirrhosis.

Patients with Renal Impairment

Dosage adjustment is not required for patients with renal impairment.

HOW SUPPLIED

Zafirlukast 10 mg Tablets, (NDC 42291-970-60) white, round, biconvex, film-coated tablets debossed with "P" on one side and "10" on the other, are supplied in opaque HDPE bottles of 60 tablets.

Zafirlukast 20 mg Tablets, (NDC 42291-971-60) white, round, biconvex, film-coated tablets debossed with "P" on one side and "20" on the other, are supplied in opaque HDPE bottles of 60 tablets.

Store at controlled room temperature, 20 to 25°C (68 to 77°F) [see USP]. Protect from light and moisture. Dispense in the original air-tight container.

PATIENT INFORMATION

Zafirlukast Tablets

Read the Patient Information leaflet before you start taking zafirlukast and each time you get a refill. There may be new information. This information does not take the place of talking to your healthcare provider about your medical condition or your treatment.

What is Zafirlukast?

Zafirlukast is a prescription medicine used to help prevent asthma attacks and for the long-term treatment of asthma symptoms in adults and children 5 years and older.

It is not known if zafirlukast is safe and effective when used in children under 5 years old. The effect of zafirlukast on growth in children has not been determined. Do not take zafirlukast if you need relief right away for a sudden asthma attack. If you get an asthma attack, you should follow the instructions your healthcare provider gave you for treating asthma attacks.

Who should not take Zafirlukast?

Do not take zafirlukast if you:

• are allergic to zafirlukast or any of the ingredients in zafirlukast. See the end of this leaflet for a complete list of ingredients in zafirlukast.

• have problems with your liver.

What should I tell my healthcare provider before taking Zafirlukast?

Before you take Zafirlukast, tell your healthcare provider if you:

• have liver problems

• have any other medical conditions

• are pregnant or plan to become pregnant. It is not known if zafirlukast will harm your unborn baby. Talk to your healthcare provider if you are pregnant or plan to become pregnant.

• are breastfeeding or plan to breastfeed. Zafirlukast can pass into your milk; it is not known whether zafirlukast may harm your baby. Women who are breastfeeding should not take zafirlukast.

Tell your healthcare provider about all the medicines you take,

including prescription and non-prescription medicines, vitamins, and herbal supplements.

Zafirlukast may affect the way other medicines work, and other medicines may affect how zafirlukast works.

Especially tell your healthcare provider if you take:

• warfarin sodium (Coumadin, Jantoven)

• erythromycin (ERYC, ERY-TAB, PCE)

• theophylline (Elixophyllin, Theo-24, Theochron, Theolair, Uniphyl)

• fluconazole (Diflucan)

Know the medicines you take. Keep a list of them to show your healthcare provider and pharmacist when you get a new medicine.

How should I take Zafirlukast?

• Take zafirlukast exactly as your healthcare provider tells you to take it.

• Take zafirlukast regularly, even if you do not have asthma symptoms.

• Do not change your dose or stop taking zafirlukast without talking to your healthcare provider.

• Do not stop taking or change the dose of your other asthma medicines unless your healthcare provider tells you to.

• Take your prescribed dose of zafirlukast by mouth at least 1 hour before or 2 hours after meals.

• Zafirlukast does not treat the symptoms of a sudden asthma attack.

• Always have a short-acting beta2-agonist medicine (rescue inhaler) with you to treat sudden symptoms. If you do not have a rescue inhaler medicine, talk to your healthcare provider to have one prescribed for you.

• If you take too much zafirlukast, call your healthcare provider or go to the nearest hospital emergency room right away.

What are the possible side effects of Zafirlukast?

Zafirlukast may cause serious side effects, including:

Severe liver problems. In some cases, these liver problems can lead to liver failure, the need for a liver transplant or death. Tell your healthcare provider right away if you have:

• pain or tenderness in the right upper side of your stomach area (abdomen)

• nausea

• tiredness

• itchiness

• yellowing of your skin or the whites of your eyes

• flu-like symptoms

• loss of appetite

• dark (tea colored) urine

• Inflammation of your blood vessels. Rarely, this can happen in people with asthma who take zafirlukast. This usually, but not always, happens in people who also take a steroid medicine by mouth that is being stopped or the dose is being lowered. Tell your healthcare provider right away if you have:

• a feeling of pins and needles or numbness of your arms or legs

• flu like symptoms

• rash

• pain and swelling of your sinuses

• Changes in behavior or mood. Tell your healthcare provider if you have changes in your behavior, problems sleeping or feel very sad.

• Hypersensitivity reactions. Tell your healthcare provider if you have severe itching, breathing problems, skin rash, skin blisters, or skin redness, or swelling.

The most common side effects of zafirlukast in people 12 years and older include:

• headache

• infection

• nausea

• diarrhea

• pain (generalized)

The most common side effects of zafirlukast in children 5 to 11 years include:

• headache

• stomach pain

Tell your healthcare provider if you have any side effect that bothers you or that does not go away.

These are not all of the possible side effects of zafirlukast. For more information, ask your healthcare provider or pharmacist.

Call your healthcare provider for medical advice about side effects. You may report side effects to FDA at 1-800-FDA-1088.

You may also report side effects to AvKARE at 1-855-361-3993.

How should I store Zafirlukast?

• Store zafirlukast at 68°F to 77°F (20°C to 25°C).

• Keep zafirlukast tablets dry.

• Keep zafirlukast in a tight closed container and keep zafirlukast out of the light.

• Keep zafirlukast and all medicines out of the reach of children.

General information about the safe and effective use of Zafirlukast.

Medicines are sometimes prescribed for purposes other than those listed in a Patient Information leaflet. Do not use zafirlukast for a condition for which it was not prescribed. Do not give zafirlukast to other people, even if they have the same symptoms that you have. It may harm them.

This Patient Information leaflet summarizes the most important information about zafirlukast. If you would like more information, talk with your healthcare provider. You can ask your pharmacist or healthcare provider for information about zafirlukast that is written for healthcare professionals.

For more information, go to www.avkare.com, or call 1-855-361-3993.

What are the ingredients in Zafirlukast?

Active ingredient: zafirlukast

Inactive ingredients: croscarmellose sodium, lactose, magnesium stearate, microcrystalline cellulose, povidone, hypromellose, and titanium dioxide.

What do Zafirlukast tablets look like?

• the 10 mg tablet is white and round with "P" marked on one side, and "10" on the other.

• the 20 mg tablet is white and round with "P" marked on one side, and "20" on the other.

Manufactured for:

AvKARE

Pulaski, TN 38478

Mfg. Rev. 12/21

AV 02/23 (W)